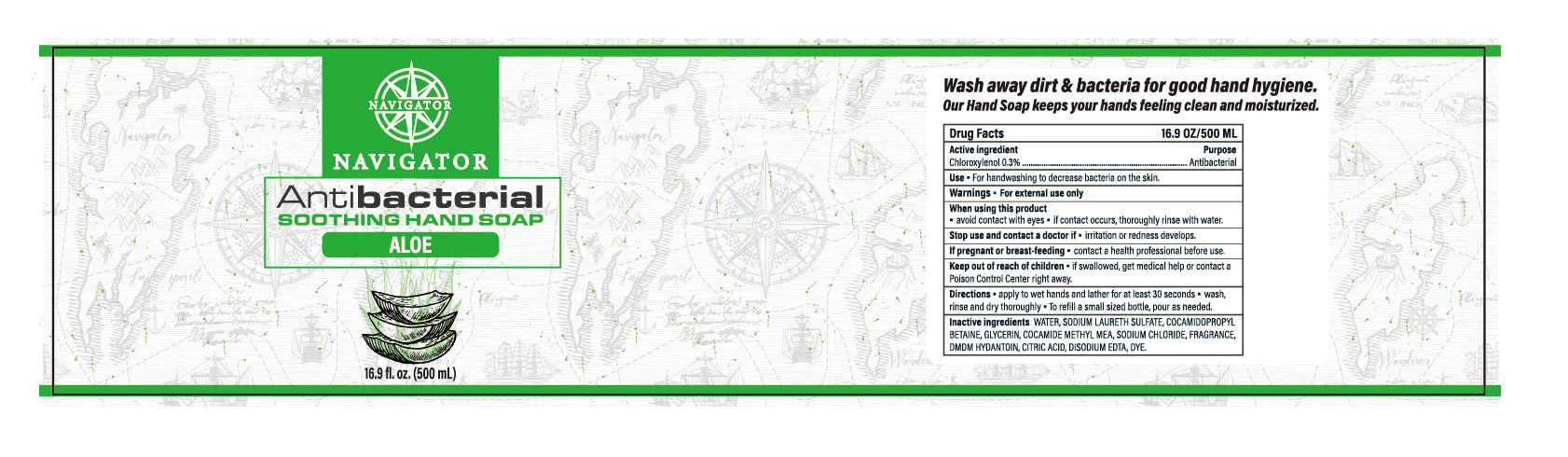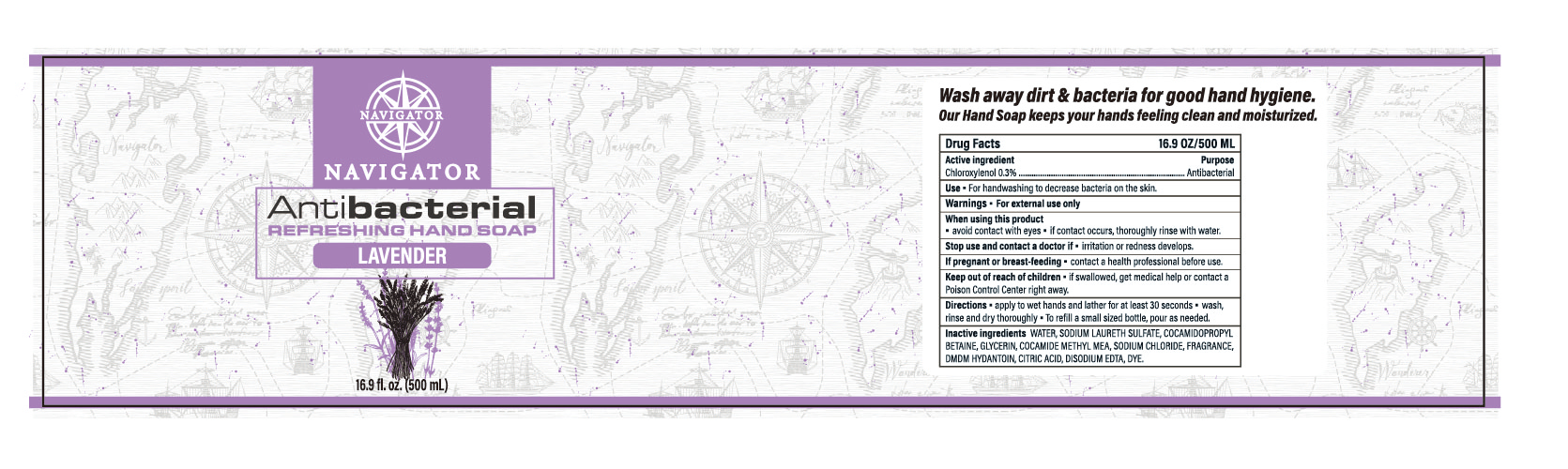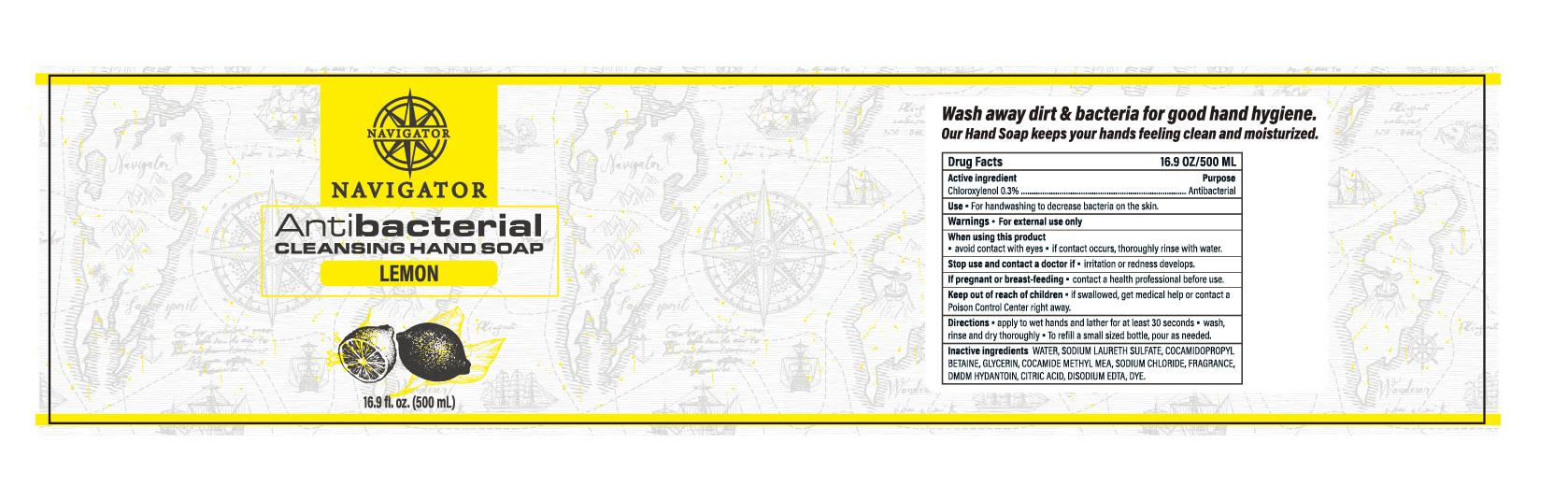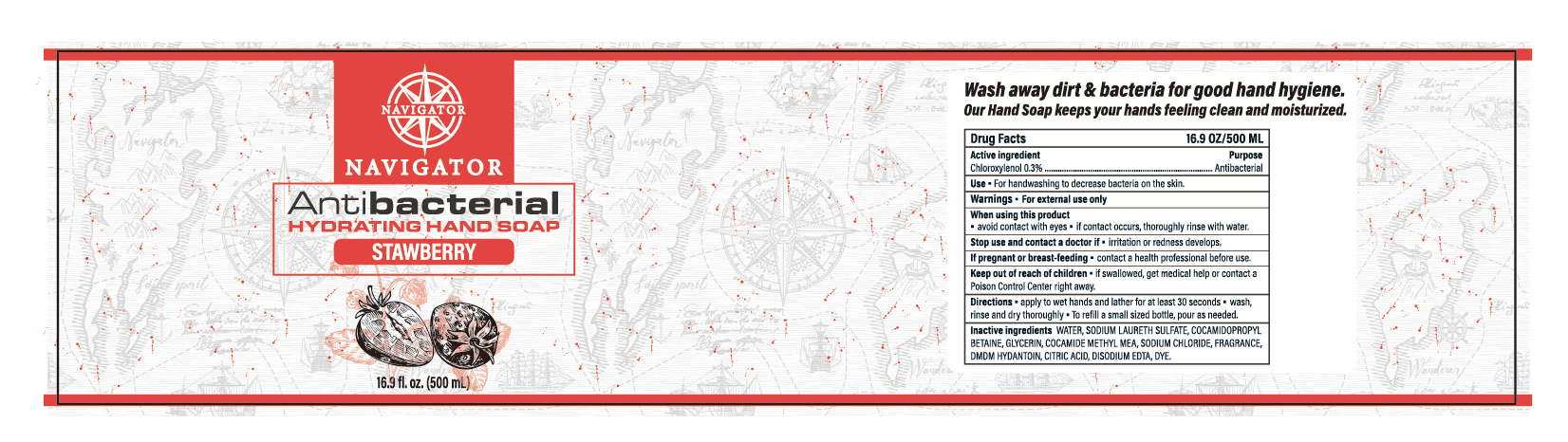 DRUG LABEL: HANDSOAP
NDC: 47993-324 | Form: GEL
Manufacturer: NINGBO JIANGBEI OCEAN STAR TRADING CO.,LTD
Category: otc | Type: HUMAN OTC DRUG LABEL
Date: 20210607

ACTIVE INGREDIENTS: CHLOROXYLENOL 0.3 g/100 mL
INACTIVE INGREDIENTS: WATER; SODIUM LAURETH SULFATE; COCAMIDOPROPYL BETAINE; GLYCERIN; COCOYL METHYL MONOETHANOLAMINE; SODIUM CHLORIDE; DMDM HYDANTOIN; ANHYDROUS CITRIC ACID; EDETATE DISODIUM

47993-324

Active ingredients

Chloroxylenol 0.3%

PURPOSE

Antibacterial

Uses：

- For hand sanitizing to reduce bacteria on the skin.

Warnings:

- For external use only.

When using this product

- avoid contact with eyes.
- if contact occurs,thoroughly rinse with water.

Stop use and ask a doctor if

- irritation or redness develops.

Keep out of reach of children

- if swallowed,get medical help or contact a Poison Control Center right away.

Directions:

- apply to wet hands and lather for at least 30 seconds.
- wash,rinse and dry thoroughly.
- To refill a small sized bottle,pour as needed.

Inactive Ingredients:

WATER, SODIUM LAURETH SULFATE, COCAMIDOPROPYL BETAINE, GLYCERIN, COCAMIDE METHYL MEA, SODIUM CHLORIDE, FRAGRANCE, DMDM HYDANTION, CITRIC ACID, DISODIUM EDTA, DYE.